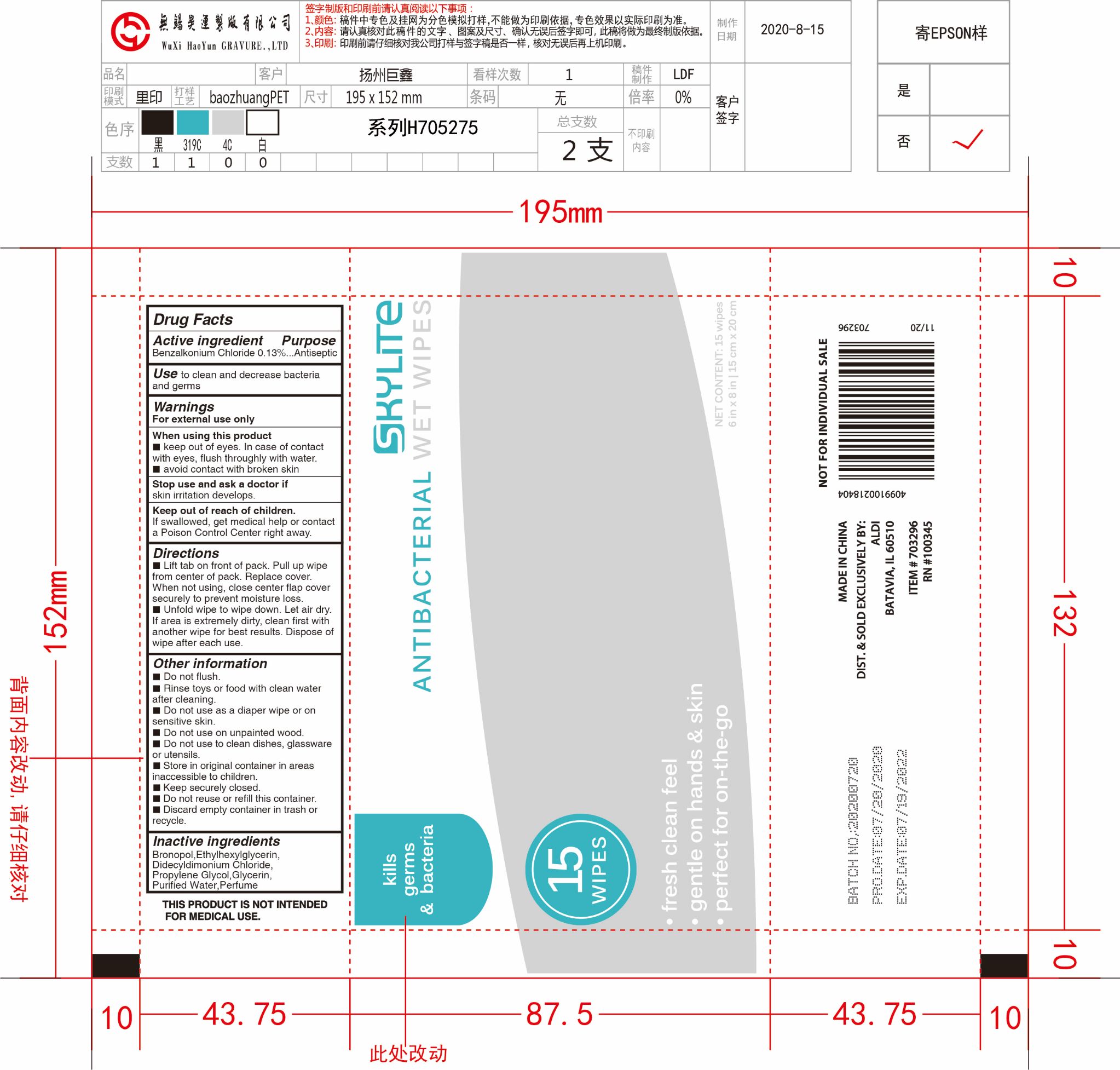 DRUG LABEL: Alcohol-free wipes
NDC: 79805-011 | Form: CLOTH
Manufacturer: JUXIN (Jiangsu) New Material Packaging Co., Ltd.
Category: otc | Type: HUMAN OTC DRUG LABEL
Date: 20221213

ACTIVE INGREDIENTS: BENZALKONIUM CHLORIDE 0.13 mg/100 mL
INACTIVE INGREDIENTS: ETHYLHEXYLGLYCERIN; WATER; GLYCERIN; PROPYLENE GLYCOL; DIDECYLDIMONIUM CHLORIDE; BRONOPOL

79805-011
Alcohol-free wipes 15pcs
79805-011-01

Active Ingredient(s)

Benzalkonium Chloride 0.13%

Purpose

Antiseptic

Use

Use to clean and decrease bacteria and germs.

Warnings

- For external use only

When using this product

- Keep out of eyes. In case of contact with eyes, flush throughly with water.
- Avoid contact with broken skin.

Stop use and ask a doctor if skin irritation develops.

Keep out of reach of children.

If swallowed, get medical help or contact a Poison Control Center right away.

Directions

- Lift tab on front of pack. Pull up wipe from center of pack. Replace cover. When not using, close center flap cover securely to prevert moisture loss.
- Unfold wipe to wipe down. Let air dry. If area is extremely dirty, clean first with another wipe for best results. Dispose of wipe after each use.

Other information

- Do not flush.
- Rinse toys or food with clean water after cleaning.
- Do not use as a diaper wipe or on sensitive skin.
- Do not use on unpainted wood.
- Do not use to clean dishes, glassware or utensils.
- Store in original container in areas inaccessible to children.
- Keep securely closed.
- Do not reuse or refill this container.
- Discard empty container in trash or recycle.

Inactive ingredients

Bronopol, Ethylhexylglycerin, Didecyldimonium Chloride, Propylene Glycol, Glycerin, Purified Water, Perfume.

Package Label - Principal Display Panel

15pcs NDC: 79805-011-01